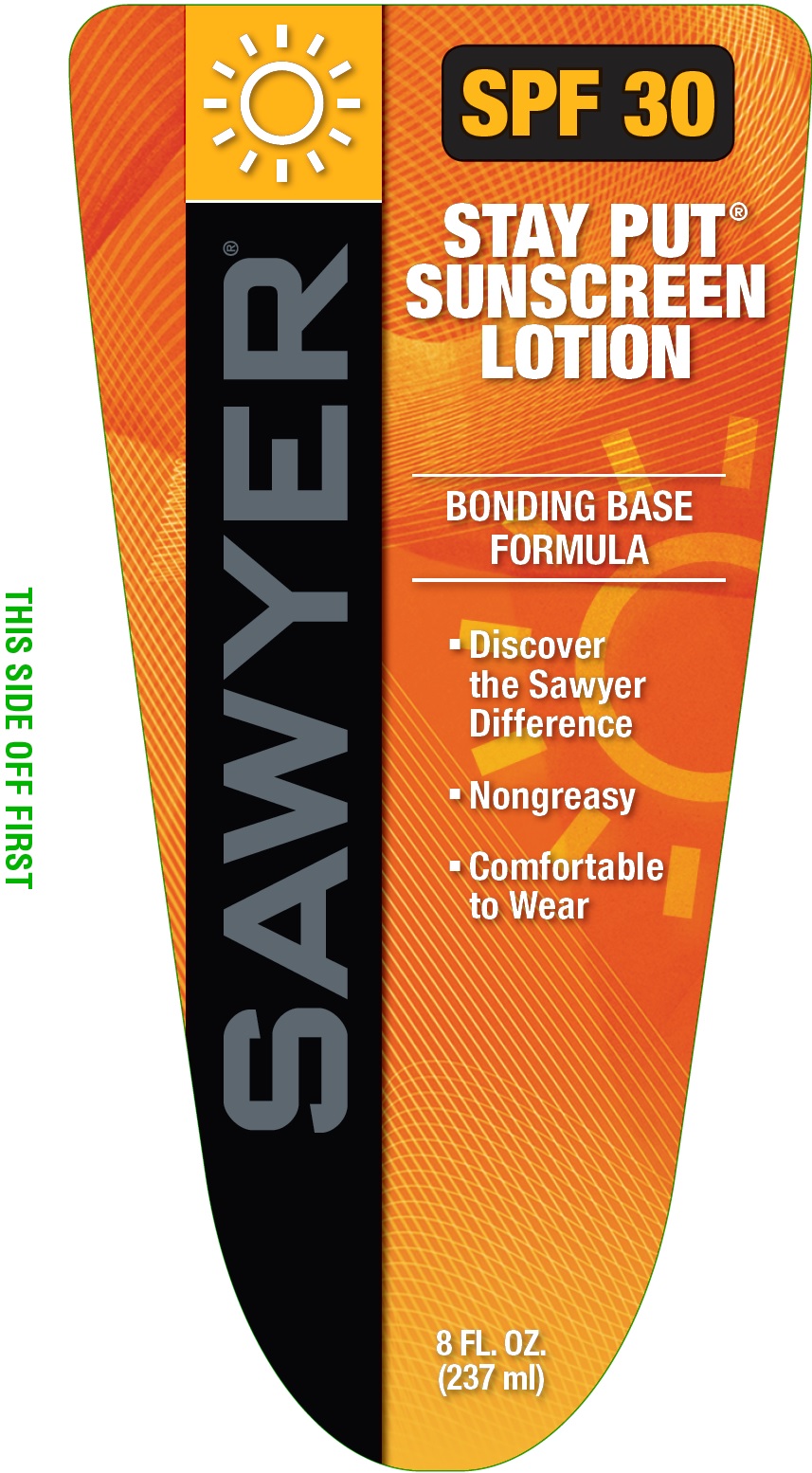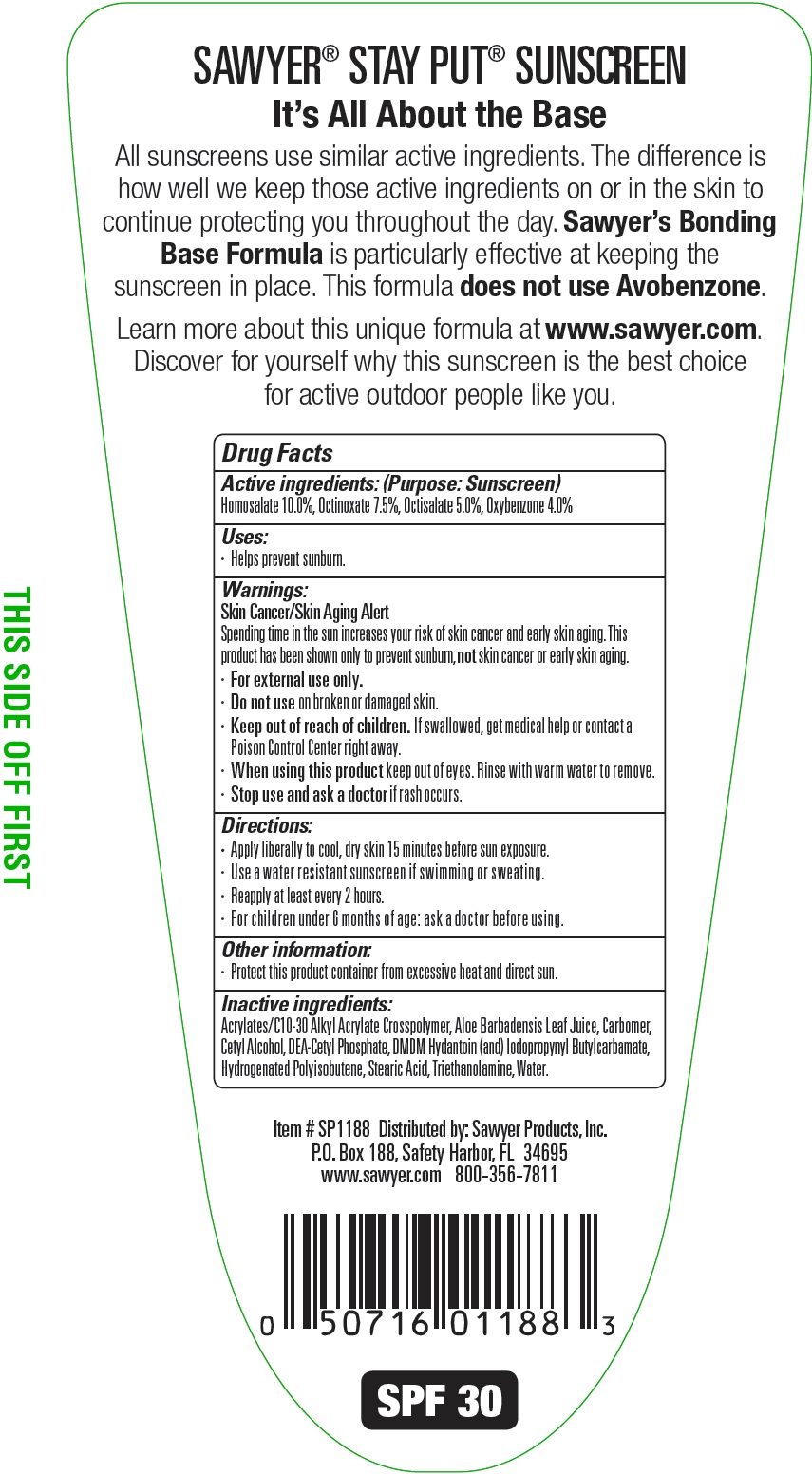 DRUG LABEL: SPF 30 Stay Put Sunscreen
NDC: 70392-012 | Form: LOTION
Manufacturer: Sawyer Products
Category: otc | Type: HUMAN OTC DRUG LABEL
Date: 20160115

ACTIVE INGREDIENTS: HOMOSALATE 100 mg/1 mL; OCTINOXATE 75 mg/1 mL; OCTISALATE 50 mg/1 mL; OXYBENZONE 40 mg/1 mL
INACTIVE INGREDIENTS: ALOE VERA LEAF; CARBOXYPOLYMETHYLENE; CETYL ALCOHOL; DIETHANOLAMINE CETYL PHOSPHATE; DMDM HYDANTOIN; IODOPROPYNYL BUTYLCARBAMATE; STEARIC ACID; TROLAMINE; WATER

SPF 30 Stay Put Sunscreen Lotion

Active ingredients:

Homosalate 10.0%, Octinoxate 7.5%, Octisalate 5.0%, Oxybenzone 4.0%

Purpose:

Sunscreen

Uses:

- Helps prevent sunburn.

Warnings:

Skin Cancer/Skin Aging Alert
Spending time in the sun increases your risk of skin cancer and early skin aging. This product has been shown only to prevent sunburn, not
skin cancer or early skin aging.

- For external use only.

Do not use

on broken or damaged skin.

Keep out of reach of children.

If swallowed, get medical help or contact a Poison Control Center right away.

When using this product

keep out of eyes. Rinse with warm water to remove.

Stop use and ask

a doctor if rash occurs.

Directions:

- Apply liberally to cool, dry skin 15 minutes before sun exposure.
- Use a water resistant sunscreen if swimming or sweating.
- Reapply at least every 2 hours.
- For children under 6 months of age: ask a doctor before using.

Other information:

- Protect this product container from excessive heat and direct sun.

Inactive ingredients:

Acrylates/C10-30 Alkyl Acrylate Crosspolymer, Aloe Barbadensis Leaf Juice, Carbomer, Cetyl Alcohol, DEA-Cetyl Phosphate, DMDM
Hydantoin (and) Iodopropynyl Butylcarbamate, Hydrogenated Polyisobutene, Stearic Acid, Triethanolamine, Water.